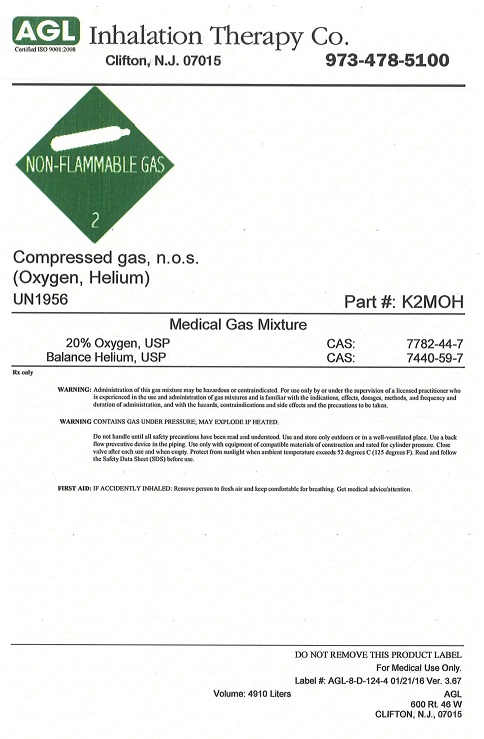 DRUG LABEL: Oxygen Helium Mixture 20/80
NDC: 17575-192 | Form: GAS
Manufacturer: AGL Inhalation Therapy Co.
Category: prescription | Type: HUMAN PRESCRIPTION DRUG LABEL
Date: 20260101

ACTIVE INGREDIENTS: OXYGEN 200 mL/1 L
INACTIVE INGREDIENTS: HELIUM 800 mL/1 L

oxygen helium 20/80

PACKAGE LABEL

AGL Certified ISO 9001:2008 Inhalation Therapy Co. CLIFTON, NJ 07015 973-478-5100
NON-FLAMMABLE GAS 2 OXYDIZER 5.1
Compressed gas, oxidizing, n.o.s. (Oxygen, Helium) UN1956 Part # K2MOH Medical Gas Mixture 20% Oxygen, USP CAS: 7782-44-7 Balance Helium, USP CAS: 7440-59-7
Rx only WARNING: Administration of this gas mixture may be hazardous or contraindicated. For use only by or under the supervision of a licensed practitioner who is experienced in the use and administration of gas mixtures and is familiar with the indications, effects, dosages, methods, and frequency and duration of administration, and with the hazards, contraindications, and side effects and the precautions to be taken. DANGER: CONTAINS GAS UNDER PRESSURE; MAY EXPLODE IF HEATED. MAY CAUSE OR INTENSIFY FIRE; OXIDIZER. Do not handle until all safety precautions have been read and understood. Keep and store away from clothing and other combustible materials. Keep valves and fittings free from grease and oil. Use and store only outdoors or in a well-ventilated place. Use a back flow preventive device in the piping. Use only with equipment of compatible materials of construction and rated for cylinder pressure. Open valve slowly. Close valve after each use and when empty. Protect from sunlight when ambient temperature exceeds 52 degrees C (125 degrees F). Read and follow the Safety Data Sheet before use. FIRST AID: IF ACCIDENTALLY INHALED: Remove person to fresh air and keep comfortable for breathing. Get medical advice/attention. DO NOT REMOVE THIS PRODUCT LABEL For Medical Use Only. Label # AGL-8-D-124-4 01/21/16 Ver. 3.67 Volume: 4910 Liters AGL 600 Rt. 46 W CLIFTON, N.J., 07015